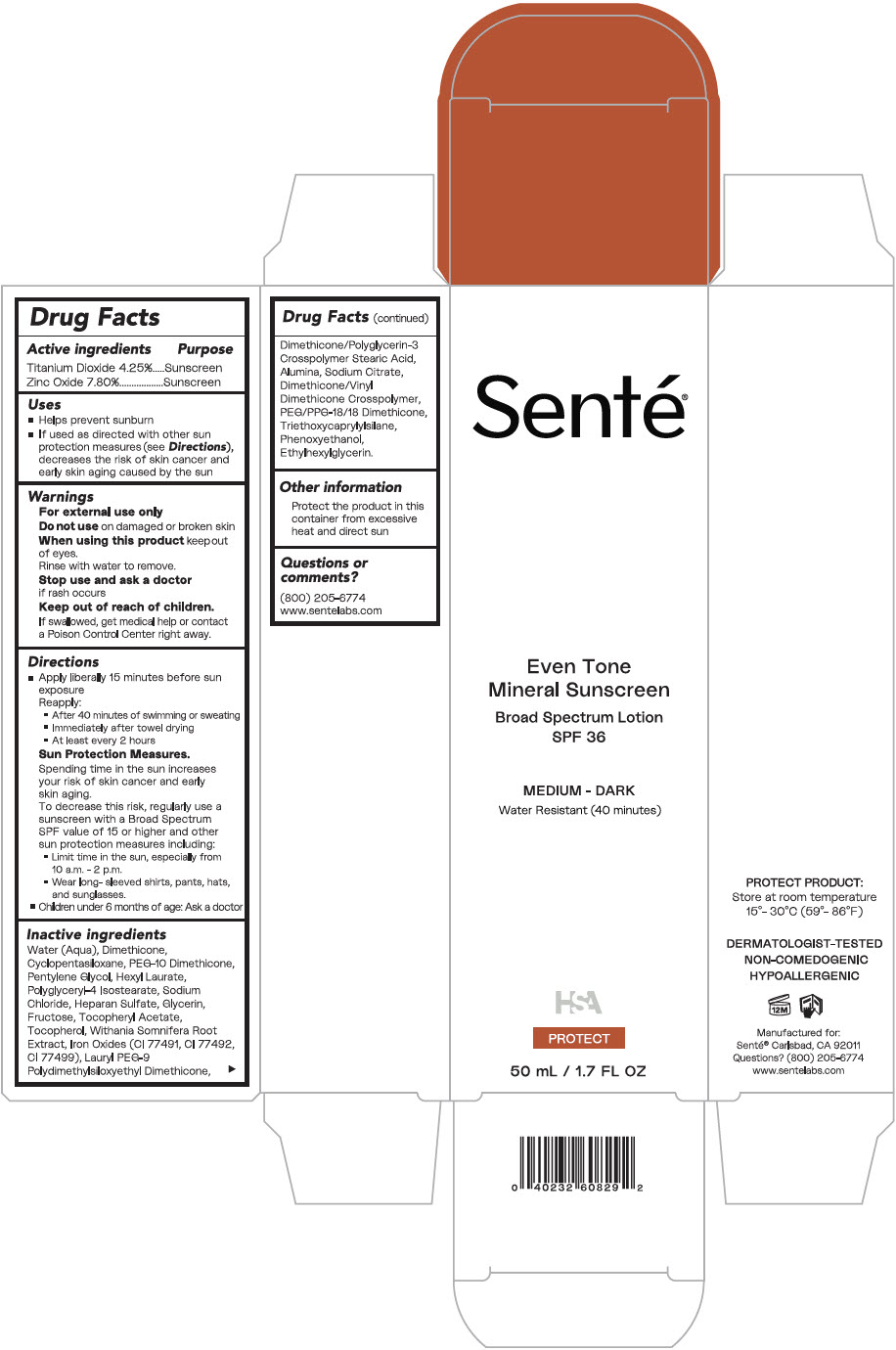 DRUG LABEL: Even Tone Mineral Sunscreen Broad Spectrum SPF 36 Medium - Dark
NDC: 71398-014 | Form: LOTION
Manufacturer: SENTÉ, Inc.
Category: otc | Type: HUMAN OTC DRUG LABEL
Date: 20240412

ACTIVE INGREDIENTS: Titanium Dioxide 47.43 mg/1 mL; Zinc Oxide 87.048 mg/1 mL
INACTIVE INGREDIENTS: Water; Dimethicone; CYCLOMETHICONE 5; PEG-10 DIMETHICONE (600 CST); Pentylene Glycol; Hexyl Laurate; FERRIC OXIDE YELLOW; Polyglyceryl-4 Isostearate; Sodium Chloride; HEPARAN SULFATE (PORCINE 5500 MW); Glycerin; Fructose; .ALPHA.-TOCOPHEROL ACETATE; Tocopherol; WITHANIA SOMNIFERA ROOT; FERRIC OXIDE RED; FERROSOFERRIC OXIDE; Lauryl PEG-9 Polydimethylsiloxyethyl Dimethicone; Stearic Acid; ALUMINUM OXIDE; SODIUM CITRATE, UNSPECIFIED FORM; DIMETHICONE/VINYL DIMETHICONE CROSSPOLYMER (SOFT PARTICLE); PEG/PPG-18/18 Dimethicone; TRIETHOXYCAPRYLYLSILANE; Phenoxyethanol; Ethylhexylglycerin

Even Tone Mineral Sunscreen Broad Spectrum SPF 36 Medium - Dark

Drug Facts

ACTIVE INGREDIENT

Active ingredients | Purpose
Titanium Dioxide 4.25% | Sunscreen
Zinc Oxide 7.80% | Sunscreen

Uses

- Helps prevent sunburn
- If used as directed with other sun protection measures (see Directions), decreases the risk of skin cancer and early skin aging caused by the sun

Warnings

For external use only

Do not use on damaged or broken skin

When using this product keep out of eyes. Rinse with water to remove.

Stop use and ask a doctor if rash occurs

Keep out of reach of children.

If swallowed, get medical help or contact a Poison Control Center right away.

Directions

- Apply liberally 15 minutes before sun exposure
- Reapply:
  - After 40 minutes of swimming or sweating
  - Immediately after towel drying
  - At least every 2 hours

Sun Protection Measures.

Spending time in the sun increases your risk of skin cancer and early skin aging. To decrease this risk, regularly use a sunscreen with a Broad Spectrum SPF value of 15 or higher and other sun protection measures including:

- Limit time in the sun, especially from 10 a.m.-2 p.m.
- Wear long- sleeved shirts, pants, hats, and sunglasses.
- Children under 6 months of age: Ask a doctor

Inactive ingredients

Water (Aqua), Dimethicone, Cyclopentasiloxane, PEG-10 Dimethicone, Pentylene Glycol, Hexyl Laurate, Polyglyceryl-4 Isostearate, Sodium Chloride, Heparan Sulfate, Glycerin, Fructose, Tocopheryl Acetate, Tocopherol, Withania Somnifera Root Extract, Iron Oxides (C.I. 77491, C.I. 77492, C.I. 77499), Lauryl PEG-9 Polydimethylsiloxyethyl Dimethicone, Dimethicone/Polyglyceryin-3 Crosspolymer, Stearic Acid, Alumina, Sodium Citrate, Dimethicone/Vinyl Dimethicone Crosspolymer, PEG/PPG-18/18 Dimethicone, Triethoxycaprylylsilane, Phenoxyethanol, Ethylhexylglycerin.

Other information

Protect the product in this container from excessive heat and direct sun

Questions or comments?

(800) 205-6774

www.sentelabs.com

PRINCIPAL DISPLAY PANEL - 50 mL Tube Carton

Senté®

Even Tone
Mineral Sunscreen

Broad Sprectrum Lotion
SPF 36

MEDIUM - DARK
Water Resistant (40 minutes)

HSA

PROTECT

50 mL / 1.7 FL OZ